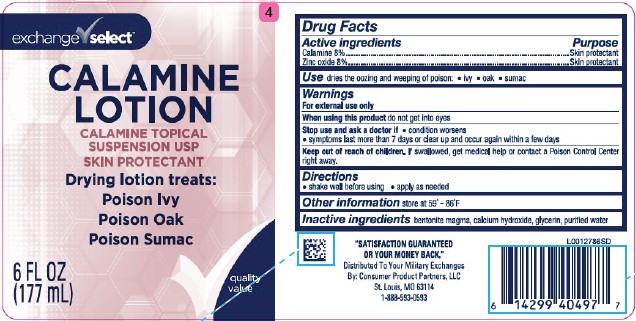 DRUG LABEL: Calamine
NDC: 55301-063 | Form: LOTION
Manufacturer: Your Military Exchanges
Category: otc | Type: HUMAN OTC DRUG LABEL
Date: 20260212

ACTIVE INGREDIENTS: FERRIC OXIDE RED 80 mg/1 mL; ZINC OXIDE 80 mg/1 mL
INACTIVE INGREDIENTS: BENTONITE; CALCIUM HYDROXIDE; GLYCERIN; WATER

Exchange Select 063.001/063AA
Calamine Lotion

Active ingredients

Calamine 8%
Zinc oxide 8%

Purpose

Skin Protectant

Use

dries the oozing and weeping of poison:

- ivy
- oak
- sumac

Warnings

For external use only

When using this product

do not get into eyes

Stop use and ask a doctor if

- condition worsens
- symptoms last more than 7 days or clear up and occur again within a few days

Keep out of reach of children.

If swallowed, get medical help or contact a Poison Control Center right away.

Directions

- shake well before using
- apply as needed

Other information

store at 59⁰ - 86⁰ F

Inactive ingredients

bentonite magma, calcium hydroxide, glycerin, purified water

Adverse Reactions

"SATISFACTION GUARANTEED OR YOUR MONEY BACK"

Distributed To Your Military Exchanges

By: Consumer Product Partners, LLC

St. Louis MO 63114

1-888-593-0593

principal display panel

Exchange Select™

CALAMINE LOTION

CALAMINE TOPICAL

SUSPENSION USP

SKIN PROTECTANT

Drying lotion treats:

Poison Ivy
Poison Oak
Poison Sumac

quality value

6 FL OZ (177 mL)